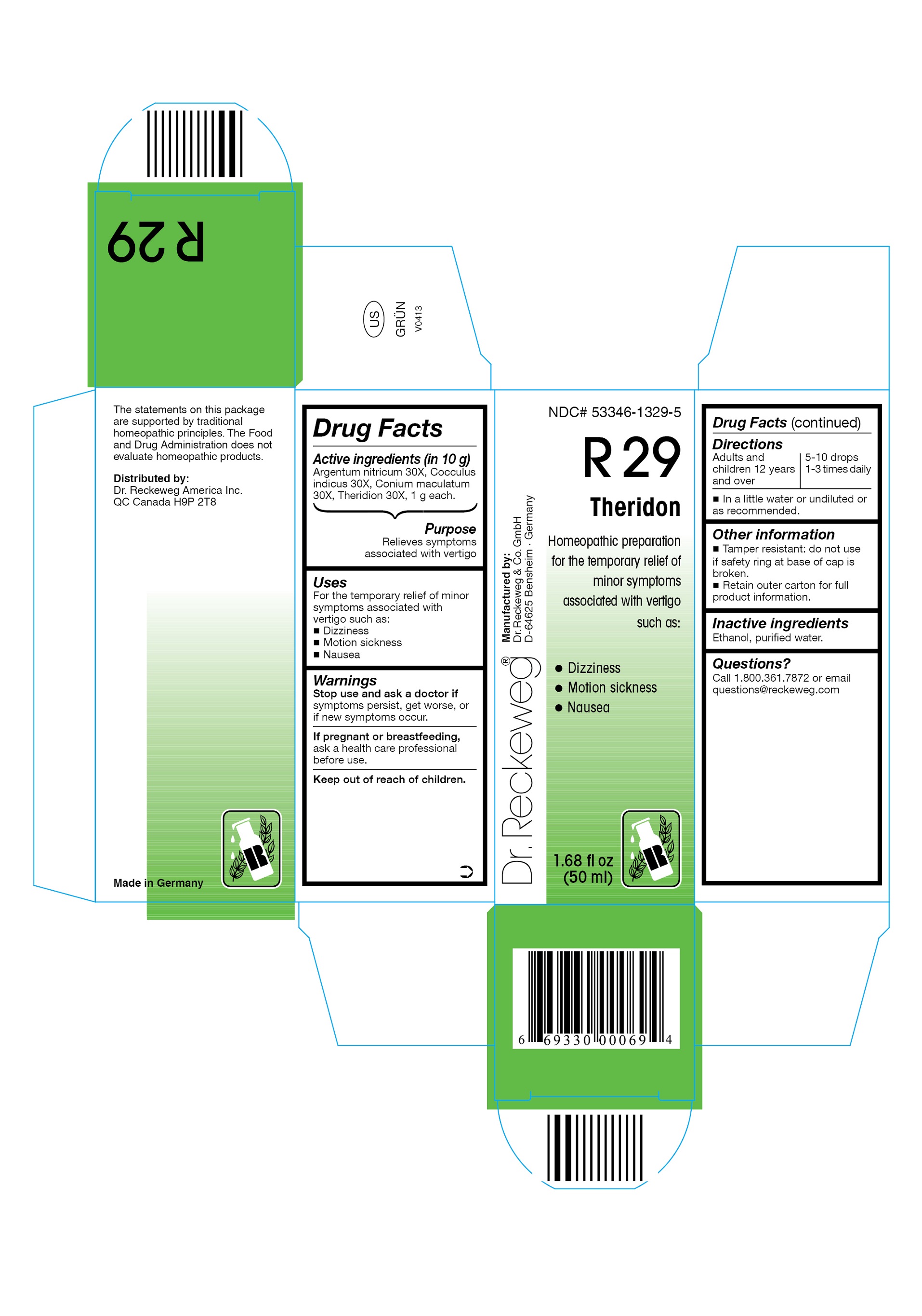 DRUG LABEL: DR. RECKEWEG R29 Theridon
NDC: 53346-1329 | Form: LIQUID
Manufacturer: PHARMAZEUTISCHE FABRIK DR. RECKEWEG & CO
Category: homeopathic | Type: HUMAN OTC DRUG LABEL
Date: 20130404

ACTIVE INGREDIENTS: SILVER NITRATE 30 [hp_X]/50 mL; ANAMIRTA COCCULUS SEED 30 [hp_X]/50 mL; CONIUM MACULATUM FLOWERING TOP 30 [hp_X]/50 mL; THERIDION CURASSAVICUM 30 [hp_X]/50 mL
INACTIVE INGREDIENTS: ALCOHOL; WATER

DR. RECKEWEG R29 Theridon

Active ingredients

Argentum nitricum 30X, Cocculus indicus 30X, Conium maculatum 30X, Theridion 30X, 1 g each in 10 g.

Purpose

Relieves symptoms associated with vertigo

Uses

For the temporary relief of minor symptoms associated with vertigo such as:

- Dizziness
- Motion sickness
- Nausea

Warnings

Stop use and ask a doctor if symptoms persist, get worse, or if new symptoms occur.

PREGNANCY OR BREAST FEEDING

If pregnant or breastfeeding, ask a health care professional before use.

Keep out of reach of children.

Directions

Adults and children ≥ 12 years 5-10 drops 1-3 times daily in a little water or undiluted or as recommended.

Other information

- Tamper resistant: do not use if safety ring at base of cap is broken.
- Retain outer carton for full product information.

Inactive ingredients

Ethanol, purified water.

Questions?

Call 1-800-361-7872 or email questions@reckeweg.com

PACKAGE LABEL

NDC# 53346-1329-5

Dr. Reckeweg R29 Theridon

Homeopathic preparation for the temporary relief of minor symptoms associated with vertigo such as:

- Dizziness
- Motion sickness
- Nausea

Manufactured by:

Dr. Reckeweg Co. GmbH

D-64625 Bensheim

Germany

1.68 fl oz
(50 ml)